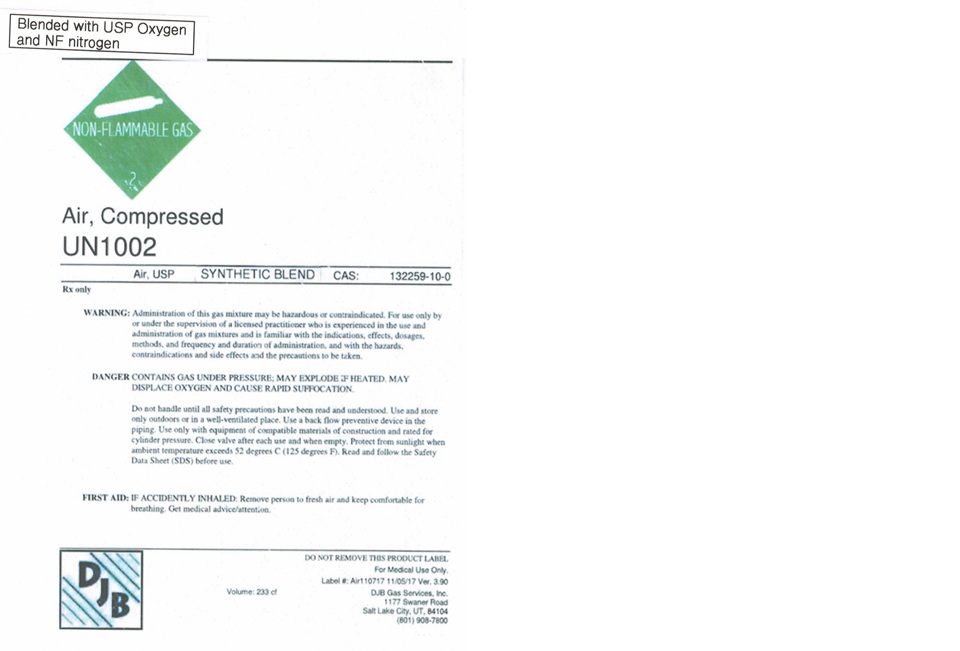 DRUG LABEL: Air
NDC: 43621-004 | Form: GAS
Manufacturer: DJB Gas Services, Inc
Category: prescription | Type: HUMAN PRESCRIPTION DRUG LABEL
Date: 20260226

ACTIVE INGREDIENTS: OXYGEN 210 mL/1 L

Air

PACKAGE LABEL

Blended with USP Oxygen and NF Nitrogen

Air, Compressed

UN1002

Air, USP SYNTHETIC BLEND CAS: 132259-10-0

Rx only

WARNING: Administration of this gas may be hazardous or contraindicated. For use only by or under the supervision of a licensed practitioner who is experienced in the use and administration of gas mixtures and is familiar with the indications, effects, dosages, methods, and frequency and duration of administration, and with the hazards, contraindications and side effects and the precautions to be taken.

DANGER CONTAINS GAS UNDER PRESSURE; MAY EXPLODE IF HEATED. MAY DISPLACE OXYGEN AND CAUSE RAPID SUFFOCATION.

Do not handle until all safety precautions have been read and understood. Use and store only outdoors or in a well-ventilated place. Use a back flow preventive device in the piping. Use only with equipment of compatible materials of construction and rated for cylinder pressure. Close valve after each use and when empty. Protect from sunlight when ambient temperature exceeds 52 degrees C (125 degrees F). Read and follow the Safety Data Sheet (SDS) before use.

FIRST AID: IF ACCIDENTLY INAHLED: Remove person to fresh air and keep comfortable for breathing. Get medical advice/attention.

DJB

Volume: 233 cf

DO NOT REMOVE THIS PRODUCT LABEL.

For Medical Use Only.

Label #: Air110717 11/05/17 Ver. 3.90

DJB Gas Services, Inc.

1177 Swaner Road

Salt Lake City, UT 84104

(801) 908-7800